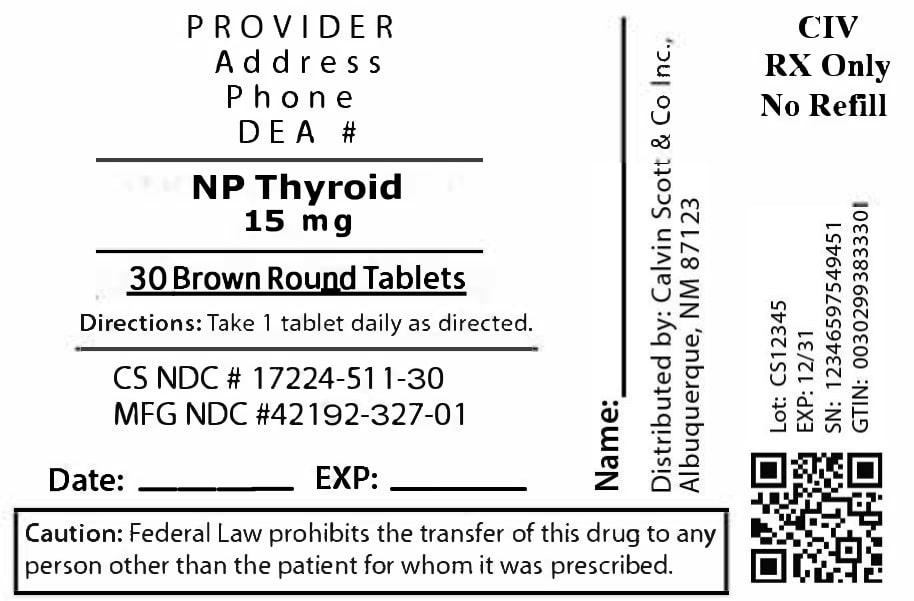 DRUG LABEL: NP Thyroid
NDC: 17224-511 | Form: TABLET
Manufacturer: Calvin Scott & Co Inc.
Category: otc | Type: HUMAN OTC DRUG LABEL
Date: 20250812

ACTIVE INGREDIENTS: LIOTHYRONINE 2.25 ug/1 1; LEVOTHYROXINE 9.5 ug/1 1
INACTIVE INGREDIENTS: DEXTROSE MONOHYDRATE; CALCIUM STEARATE; MALTODEXTRIN; MINERAL OIL

DOSAGE AND ADMINISTRATION

Take 1 tablet daily on an empty stomach or as directed.

WARNINGS

Do not exceed recommended dose. Keep out of reach of children.

INACTIVE INGREDIENT

Calcium stearate, dextrose, maltodextrin, mineral oil, modified wheat starch

INDICATIONS AND USAGE

Used as a thyroid hormone replacement for hypothyroidism.

PURPOSE

Thyroid hormone replacement

ACTIVE INGREDIENT

Thyroid 15 mg

Keep out of reach of children. In case of accidental overdose, contact a doctor or Poison Control Center immediately.

17224-511-30

Package label for NP Thyroid 15 mg tablets (30 tablets per bottle). Contains product name, dosage strength, NDC 17224-511-30, manufacturer/repacker name, and usage instructions as printed on the label.